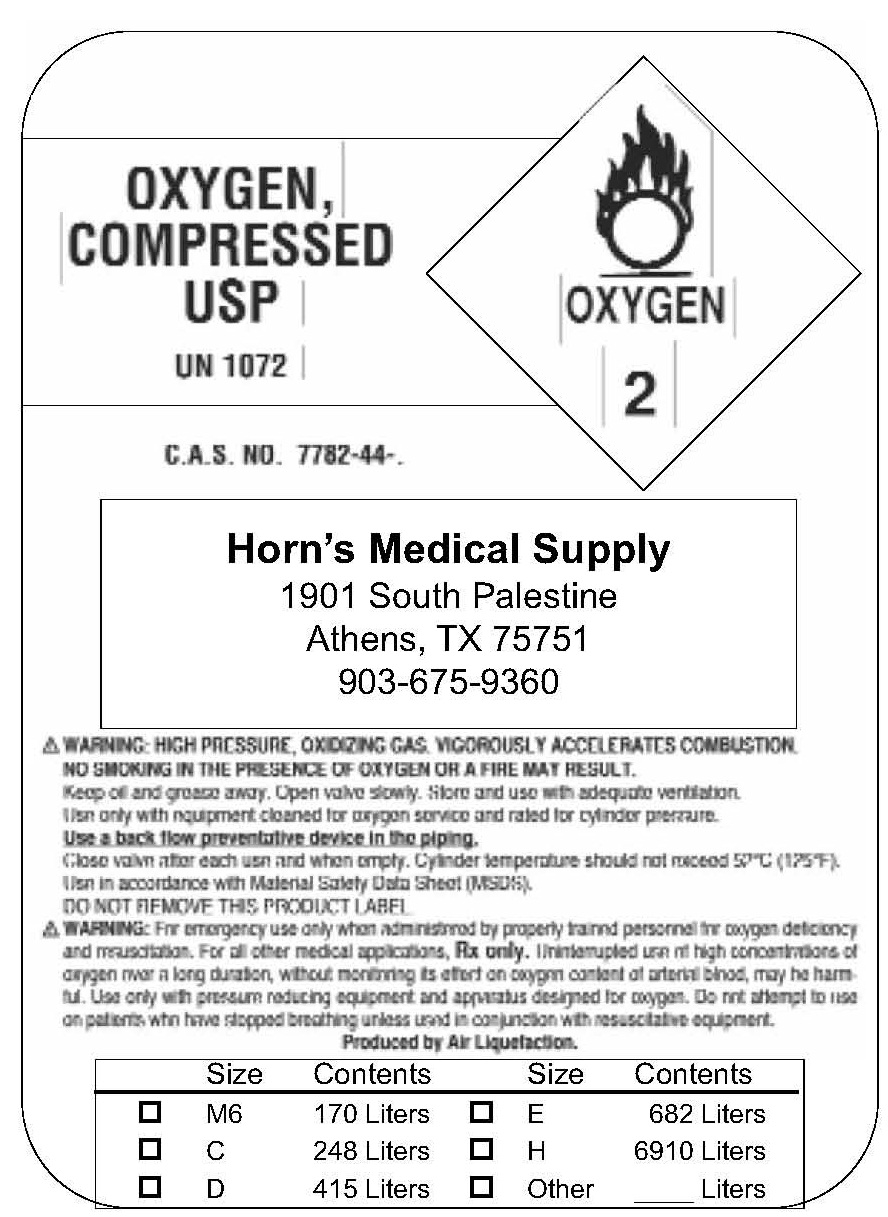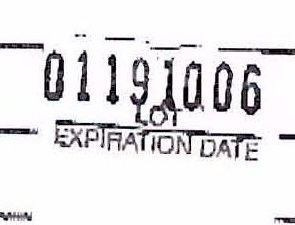 DRUG LABEL: Oxygen
NDC: 50577-0001 | Form: GAS
Manufacturer: Horn's Medical Supply, Inc.
Category: prescription | Type: HUMAN PRESCRIPTION DRUG LABEL
Date: 20100226

ACTIVE INGREDIENTS: Oxygen 99 L/100 L

Oxygen